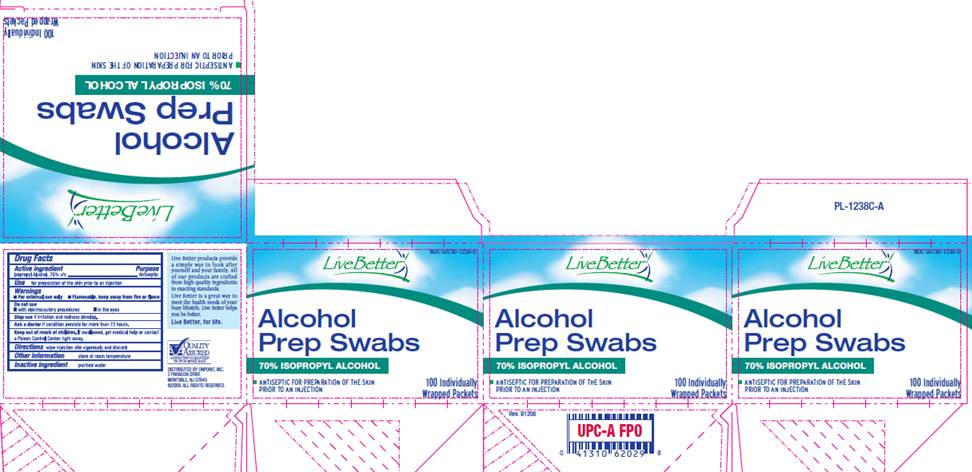 DRUG LABEL: Isopropyl Alcohol Prep Swab
NDC: 50730-1238 | Form: SWAB
Manufacturer: H and P Industries, Inc. dba Triad Group
Category: otc | Type: HUMAN OTC DRUG LABEL
Date: 20091211

ACTIVE INGREDIENTS: Isopropyl alcohol .7 mL/1 1
INACTIVE INGREDIENTS: water

DRUG FACTS

ACTIVE INGREDIENT

Isopropyl Alcohol 70% v/v

PURPOSE

Antiseptic

USE

For preparation of the skin prior to an injection

WARNINGS

For external use only.
Flammable, keep away from fire or flame.

Do not use

- with electrocautery procedures
- in the eyes

Stop use

if irritation and redness develop.

Ask a doctor

if condition persists for more than 72 hours.

Keep out of reach of children

If swallowed, get medical help or contact a Poison Control Center right away.

DIRECTIONS

Wipe injection site vigorously and discard

OTHER INFORMATION

Store at room temperature

INACTIVE INGREDIENT

purified water

PACKAGE INFORMATION

NDC 50730-1238-0
Live Better
Alcohol
Prep Swabs
70% Isopropyl Alcohol
ANTISEPTIC FOR PREPARATION OF THE SKIN PRIOR TO AN INJECTION
100 Individually Wrapped Packets
Live Better products provide a simple way to look after yourself and your family. All of our products are crafted from high quality ingredients to exacting standards.
Live Better is a great way to meet the health needs of your busy lifestyle. Live Better helps you be better.
Live Better, for life.
DISTRIBUTED BY ONPOINT, INC.
2 PARAGON DRIVE
MONTVALE, NJ 07645
©2009 ALL RIGHTS RESERVED.